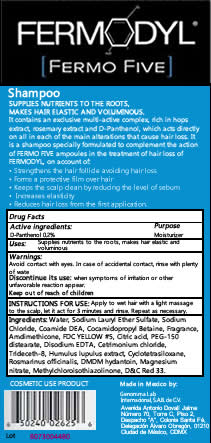 DRUG LABEL: FERMODYL
NDC: 51769-505 | Form: SHAMPOO
Manufacturer: All Natural Dynamics
Category: otc | Type: HUMAN OTC DRUG LABEL
Date: 20201219

FERMODYL FERMO 5

Application:

Apply to wet hair with a light massage to the scalp, let it act for 3 minutes and rinse. Repeat as necessary.

Precautions:

Avoid contact with eyes. In case of accidental contact, rinse with plenty of water. Discontinue its use when symptoms of irritation or other unfavorable reaction appear.

Inactive Ingredients:

Water, Sodium Lauryl Ether Sulfate, Sodium Chloride, Coamide DEA, Cocamidopropyl Betaine, Fragrance, Amdimethicone, FDC YELLOW #5, Citric acid, PEG-150 distearate, Disodium EDTA,, Cetrimonium chloride, Trideceth-8, Humulus lupulus extract, Cyclotetrasiloxane, Rosmarinus officinalis, DMDM hydantoin, Magnesium nitrate, Methylchloroisothiazolinone, D&C Red 33.

Warning:

Keep out of reach of childeren.

Purpose:

SUPPLIES NUTRIENTS TO THE ROOTS, AND MAKES HAIR ELASTIC AND VOLUMINOUS.

Active Ingredients:

Pathenol 0.002 mL per 1 ML

Indications:

For external use only